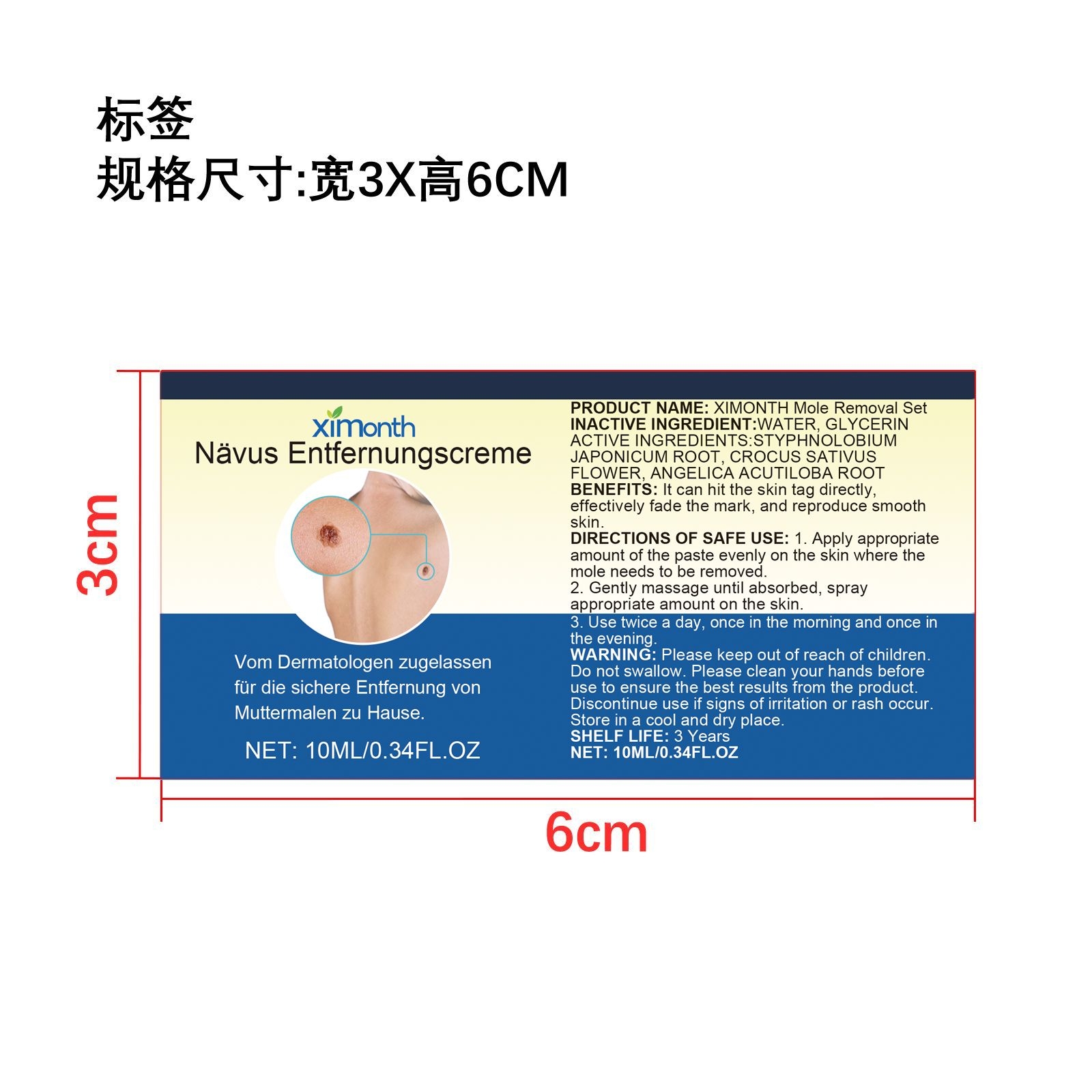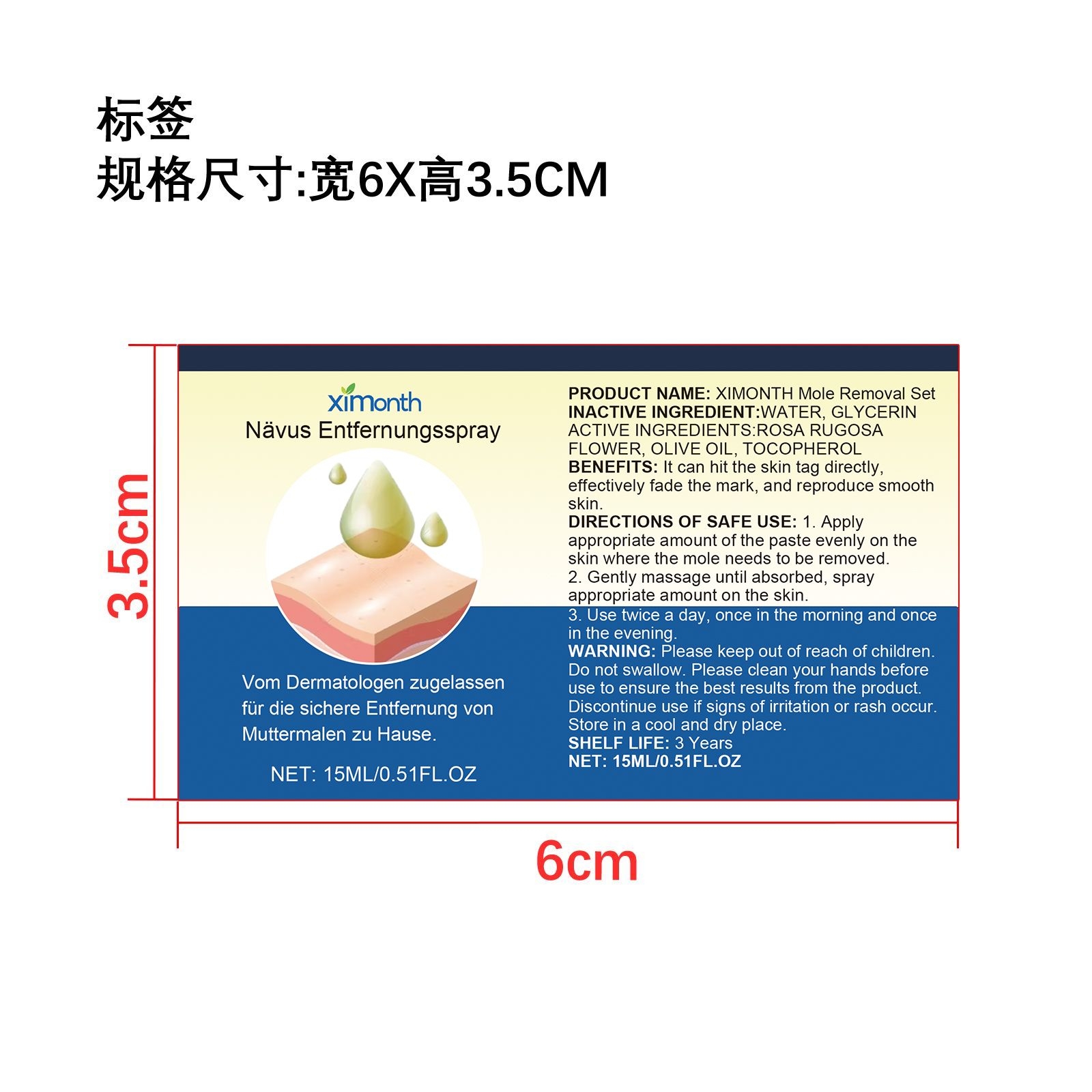 DRUG LABEL: NAVUS ENTFERNUNGSCREME
NDC: 84660-042 | Form: LIQUID
Manufacturer: Guangdong Ximonth Technology Co., Ltd.
Category: otc | Type: HUMAN OTC DRUG LABEL
Date: 20241016

ACTIVE INGREDIENTS: STYPHNOLOBIUM JAPONICUM ROOT 1.5 mg/10 mg; CROCUS SATIVUS FLOWER 1.5 mg/10 mg; ANGELICA ACUTILOBA ROOT 3 mg/10 mg
INACTIVE INGREDIENTS: WATER 3 mg/10 mg; GLYCERIN 1 mg/10 mg

ACTIVE INGREDIENTS

NAVUS ENTFERNUNGSCREME:STYPHNOLOBIUM JAPONICUM ROOT, CROCUS SATIVUS FLOWER, ANGELICA ACUTILOBA ROOT

NÄVUS ENTFERNUNGSSPRAY: ROSA RUGOSA FLOWER, OLIVE OIL, TOCOPHEROL

PURPOSE

It can hit the skin tag directly, effectively fade the mark, and reproduce smooth skin.

USE

1. Apply appropriate amount of the paste evenly on the skin where the mole needs to be removed.

2. Gently massage until absorbed, spray appropriate amount on the skin.

3. Use twice a day, once in the morning and once in the evening.

WARNING

WARNING: Please keep out of reach of children. Do not swallow. Please clean your hands before use to ensure the best results from the product. Discontinue use if signs of irritation or rash occur. Store in a cool and dry place.

DO NOT USE

Discontinue use if signs of irritation or rash occur.

STOP USE

Discontinue use if signs of irritation or rash occur.

Please keep out of reach of children

STORAGE AND HANDLING

Store in a cool and dry place.

INACTIVE INGREDIENT

WATER, GLYCERIN